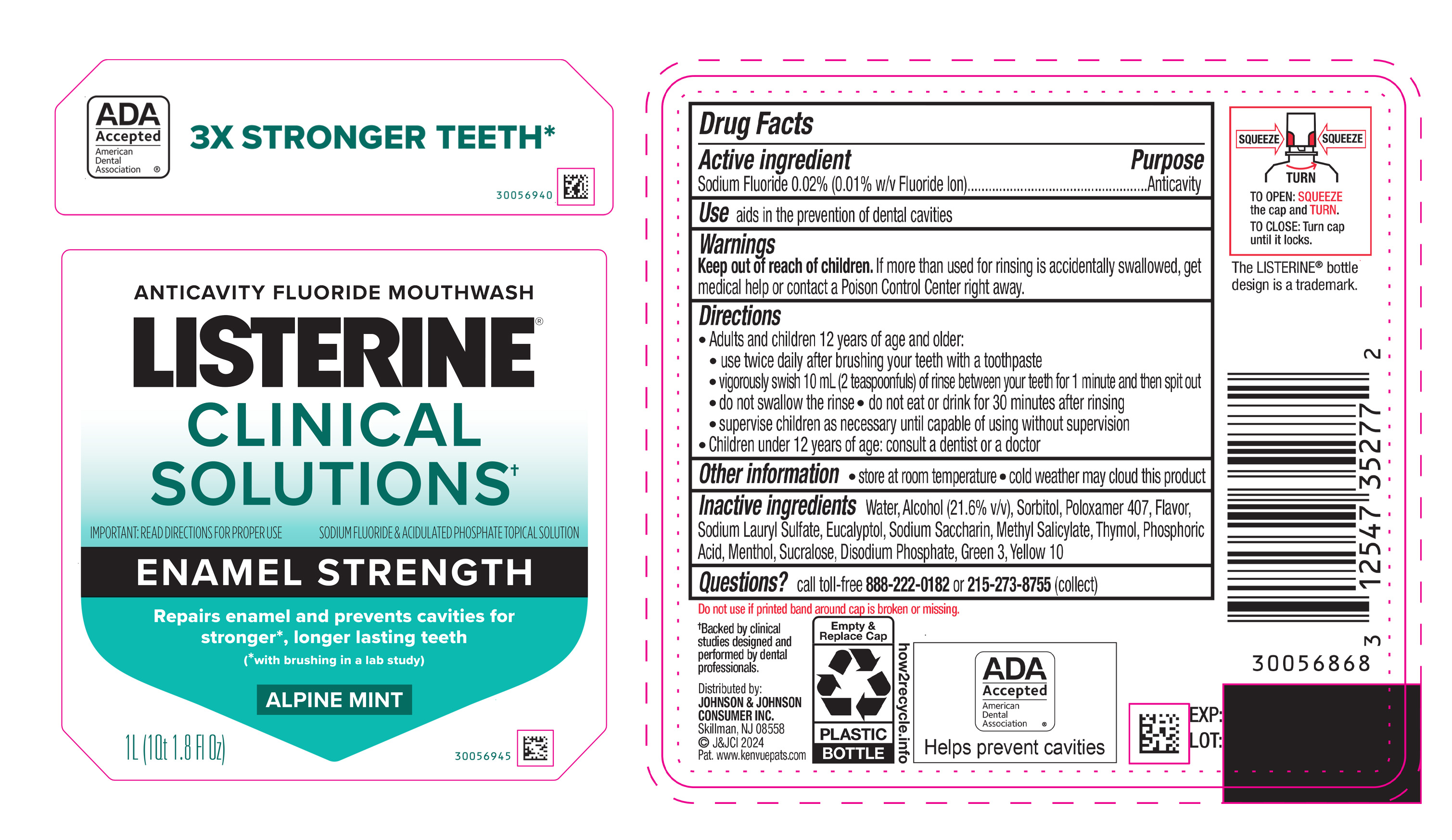 DRUG LABEL: Listerine Clinical Solutions Enamel Strength Alpine Mint
NDC: 69968-0881 | Form: MOUTHWASH
Manufacturer: Kenvue Brands LLC
Category: otc | Type: HUMAN OTC DRUG LABEL
Date: 20250422

ACTIVE INGREDIENTS: SODIUM FLUORIDE 0.1 mg/1 mL
INACTIVE INGREDIENTS: D&C YELLOW NO. 10; WATER; ALCOHOL; SORBITOL; POLOXAMER 407; SODIUM LAURYL SULFATE; PHOSPHORIC ACID; SODIUM PHOSPHATE, DIBASIC, ANHYDROUS; SUCRALOSE; SACCHARIN SODIUM; FD&C GREEN NO. 3; EUCALYPTOL; MENTHOL; METHYL SALICYLATE; THYMOL

Listerine Clinical Solutions Enamel Strength Alpine Mint

Drug Facts

Active ingredient

Sodium Fluoride 0.02% (0.01% w/v Fluoride Ion)

Purpose

Anticavity

Uses

aids in the prevention of dental cavities

Warnings

Keep out of reach of children. If more than used for rinsing is accidentally swallowed, get medical help or contact a Poison Control Center right away.

Directions

Adults and children 12 years of age and older:

- use twice daily after brushing your teeth with a toothpaste
- vigorously swish 10 mL (2 teaspoonfuls) of rinse between your teeth for 1 minute and then spit out
- do not swallow the rinse
- do not eat or drink for 30 minutes after rinsing
- supervise children as necessary until capable of using without supervision

Children under 12 years of age: consult a dentist or a doctor

Other information

- store at room temperature
- cold weather may cloud this product

Inactive ingredients

Water, Alcohol (21.6% v/v), Sorbitol, Poloxamer 407, Flavor, Sodium Lauryl Sulfate, Eucalyptol, Sodium Saccharin, Methyl Salicylate, Thymol, Phosphoric Acid, Menthol, Sucralose, Disodium Phosphate, Green 3, Yellow 10

Questions?

call toll-free 888-222-0182 or 215-273-8755 (collect)

Distributed by:
JOHNSON & JOHNSON CONSUMER INC.
Skillman, NJ 08558

PRINCIPAL DISPLAY PANEL - 1 L Bottle Label

ANTICAVITY FLUORIDE MOUTHWASH

LISTERINE®

CLINICAL

SOLUTIONS†

IMPORTANT: READ DIRECTIONS FOR PROPER USE

SODIUM FLUORIDE & ACIDULATED PHOSPHATE TOPICAL SOLUTION

ENAMEL STRENGTH

Repairs enamel and prevents cavities for

stronger*, longer lasting teeth

(*with brushing in a lab study)

ALPINE MINT

1L (1 Qt 1.8 Fl Oz)